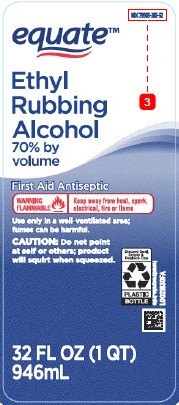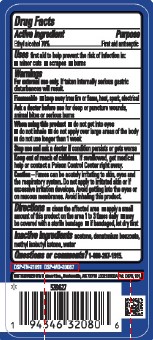 DRUG LABEL: Ethyl Alcohol
NDC: 79903-283 | Form: LIQUID
Manufacturer: Walmart Inc.
Category: otc | Type: HUMAN OTC DRUG LABEL
Date: 20260227

ACTIVE INGREDIENTS: ALCOHOL 70 mL/100 mL
INACTIVE INGREDIENTS: ACETONE; WATER; DENATONIUM BENZOATE; METHYL ISOBUTYL KETONE

Equate 876.002/876AC
Ethyl Rubbing Alcohol 70%

Active ingredient

Ethyl alcohol 70%

Purpose

First aid antiseptic

Uses

first aid to help prevent the risk of infection in:

- minor cuts
- scrapes
- burns

Warnings

For external use only.If taken internally serious gastric disturbances will result.

Flammable

- keep away from fire or flame, heat spark, electrical

Ask a doctor before use

for deep or puncture wounds, animal bites or serious burns

When using this product

- do not get into eyes
- do not inhale
- do not apply over large areas of the body
- do not use longer than 1 week

Stop use and ask a doctor if

condition persists or gets worse

Keep out of reach of children.

If swallowed, get medical help or contact a Poison Control Center right away.

Caution

Fumes can be acutely irritating to skin, eyes and the respiratory system. Do not apply to irritated skin or if excessive irritation develops. Avoid getting into the eyes or on mucous membranes. Avoid inhaling this product.

Directions

- clean the affected area
- apply a small amount of this product on the area 1 to 3 times daily
- may be covered with a sterile bandage
- if bandaged, let dry first

Inactive ingredients

acetone, denatonium benzoate, methyl isobutyl ketone, water

Questions or comments?

1-800-287-1915

Adverse event

DSP-TN-21091 DSP-MO-20087

DISTRIBUTED BY: Walmart, Inc., Bentonville, AR 72718

Pat. D675,101

PRINCIPAL DISPLAY PANEL

NDC 79903-283-32

equate™

Ethyl Rubbing Alcohol

70% by volume

First Aid Antiseptic

WARNING FLAMMABLE - Keep away from heat, spark, electrical, fire or flame

Use only in a well-ventilated are; fumes can be harmful.

CAUTION: Do not point at self or others; product will squirt when squeezed.

Discard Seal, Empty, & Replace Cap

PLASTIC BOTTLE

how2recycle.info

32 FL OZ (1 QT) 946 mL